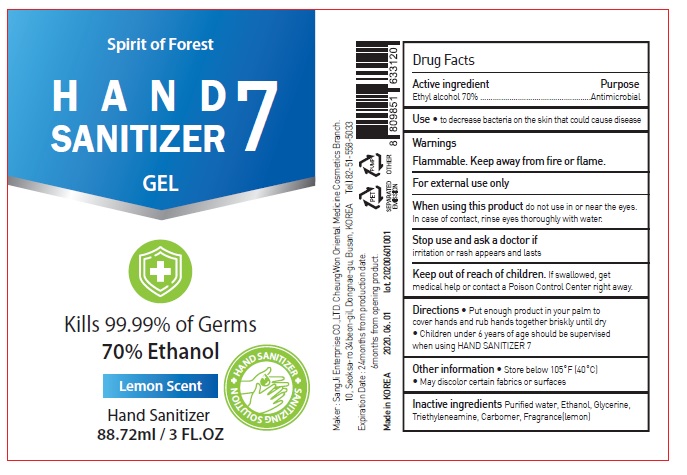 DRUG LABEL: Hand Sanitizer 7
NDC: 75695-0005 | Form: GEL
Manufacturer: Sangji Enterprise Co.,LTD Cheongwon Oriental Medical Cosmetic Branch
Category: otc | Type: HUMAN OTC DRUG LABEL
Date: 20200629

ACTIVE INGREDIENTS: ALCOHOL 0.7 mL/1 mL
INACTIVE INGREDIENTS: WATER; GLYCERIN; TROLAMINE; CARBOMER COPOLYMER TYPE A (ALLYL PENTAERYTHRITOL CROSSLINKED)

75695-0005_Hand Sanitizer 7

Active ingredient

Ethyl alcohol 70%

Purpose

Antimicrobial

Use

- To decrease bacteria on skin that could cause disease

Warnings

Flammable. Keep away from fire or flame.

For external use only

When using this product do not use in or near the eyes. In case of contact, rinse eyes thoroughly with water.

Stop use and ask a doctor if irritation or rash appears and lasts

Keep out of reach of children.

Other information

- Store below 105°F (40°C)
- May discolor certain fabrics or surfaces

Directions

Put enough product in you palm to cover hands and rub hands together briskly until dry.

Children under 6 years of age should be supervised when using HAND SANITIZER 7.

Inactive ingredients

Water, Gycerin, Triethyleneamine, Carbomer, Fragrance